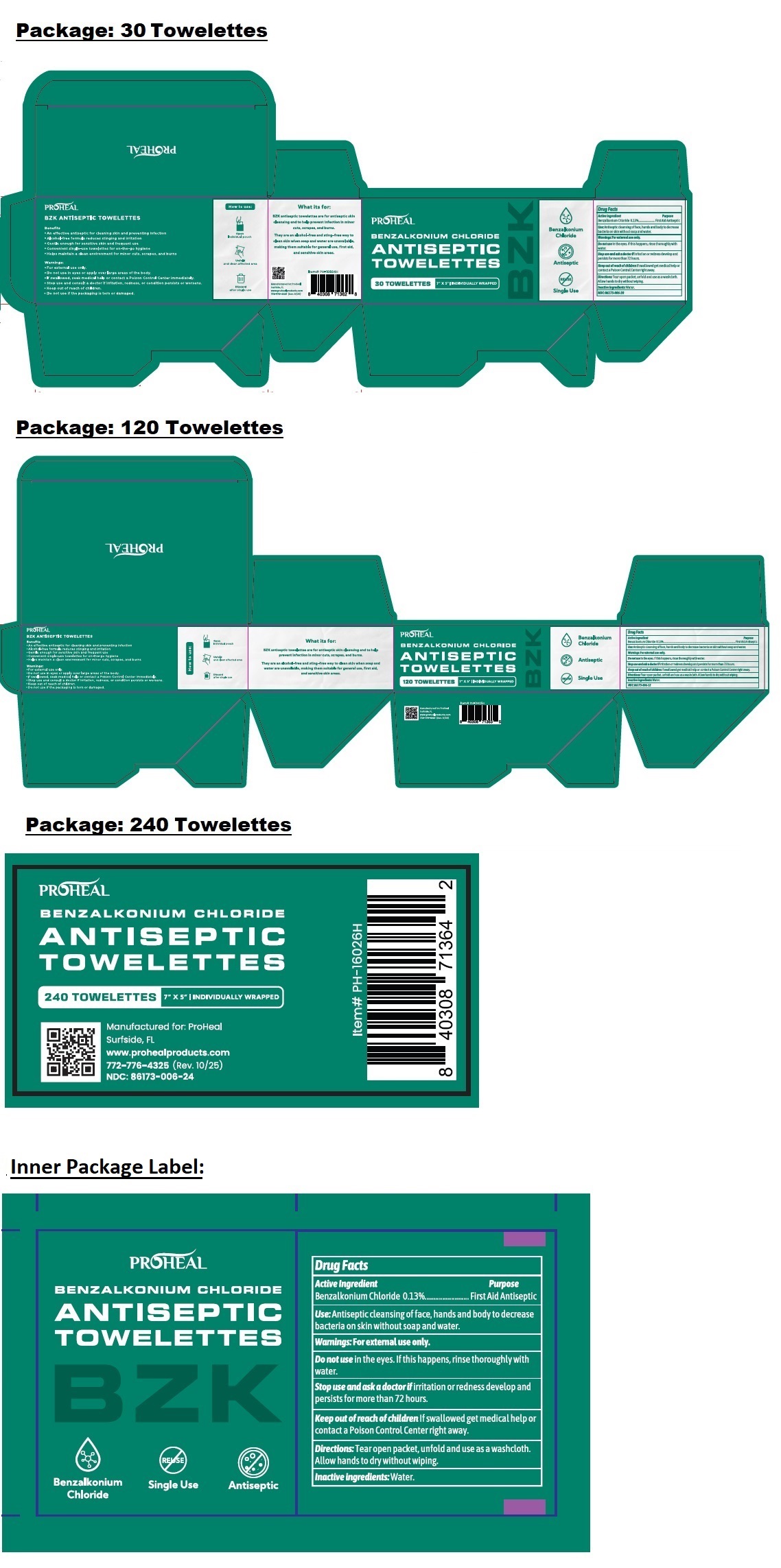 DRUG LABEL: PROHEAL BENZALKONIUM CHLORIDE ANTISEPTIC TOWELETTES
NDC: 86173-006 | Form: CLOTH
Manufacturer: Click Industries LLC
Category: otc | Type: HUMAN OTC DRUG LABEL
Date: 20251028

ACTIVE INGREDIENTS: BENZALKONIUM CHLORIDE 0.13 g/100 mL
INACTIVE INGREDIENTS: WATER

PROHEAL BENZALKONIUM CHLORIDE ANTISEPTIC TOWELETTES

Active ingredient

Benzalkonium Chloride 0.13%

Purpose

First Aid Antiseptic

Use:

Antiseptic cleansing of face, hands and body to decrease bacteria on skin without soap and water.

Warnings:

For external use only.

Do not use in the eyes. If this happens, rinse thoroughly with water.

Stop use and ask a doctor if irritation or redness develop and persists for more than 72 hours.

Keep out of reach of children if swallowed get medical help or contact a Poison Control Center right away.

Directions:

Tear open packet, unfold and use a washcloth. Allow hands to dry without wiping.

Inactive ingredients:

Water.

7" x 5" INDIVIDUALLY WRAPPED

Single Use

Benefits
• An effective antiseptic for cleaning skin and preventing infection
• Alcohol-free formula reduces stinging and irritation
• Gentle enough for sensitive skin and frequent use
• Convenient single-use towelettes for on-the-go hygiene
• Helps maintain a clean environment for minor cuts, scrapes and burns

Warnings:
• Do not use in eyes or apply over large areas of the body.
• Do not use if the packaging is torn or damaged.

What its for:

BZK antiseptic towelettes are for antiseptic skin cleansing and to help prevent infection in minor cuts, scrapes, and burns.

They are an alcohol-free and sting-free way to clean the skin when soap and water are unavailable, making them suitable for general use, first aid, and sensitive skin areas.

Manufactured for: ProHeal
Surfside, FL

www.prohealproducts.com

772-776-4325